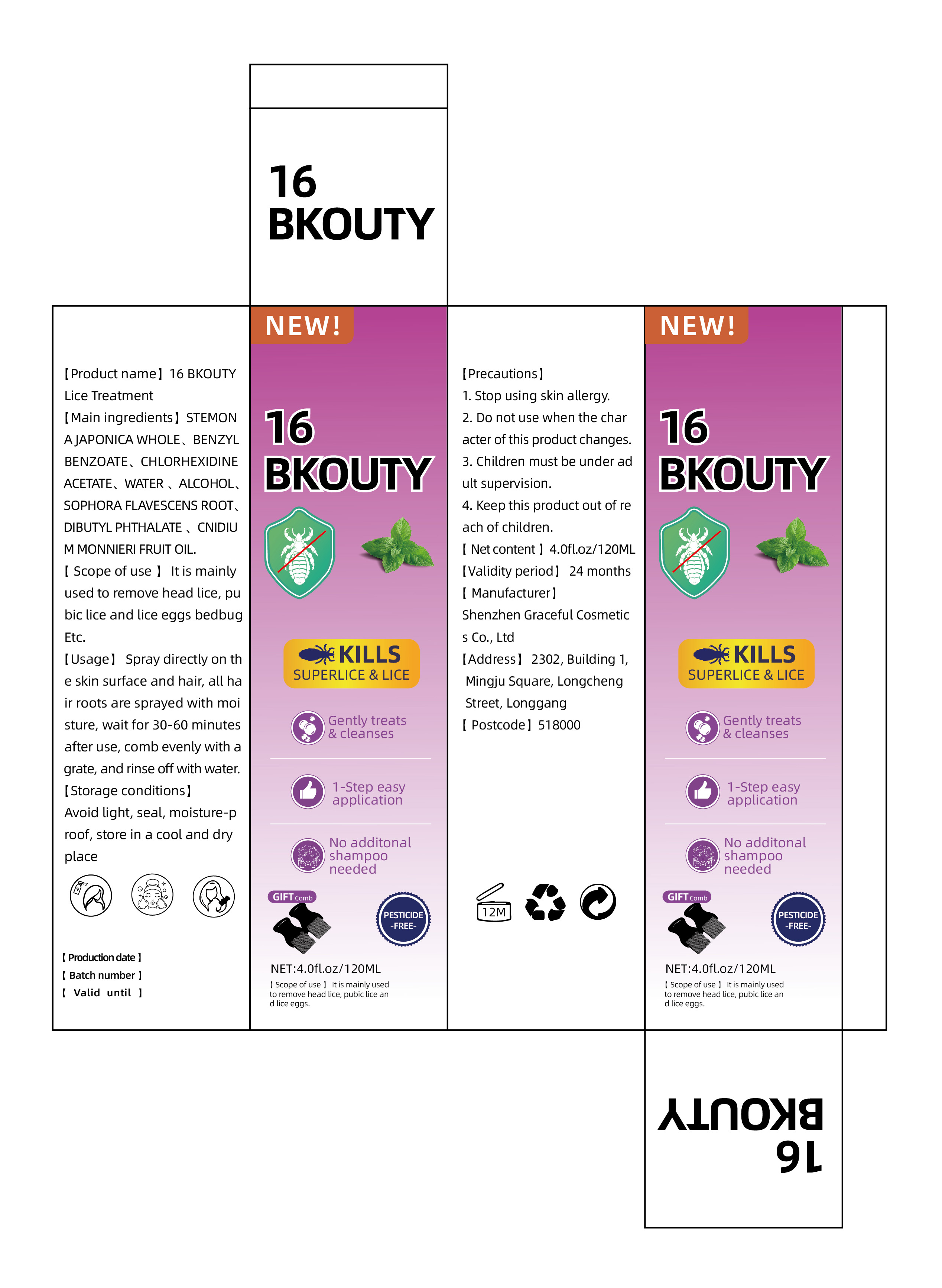 DRUG LABEL: 16BKOUTY Lice Treatment
NDC: 84422-102 | Form: LIQUID
Manufacturer: Shenzhen Graceful Cosmetics Co., Ltd
Category: otc | Type: HUMAN OTC DRUG LABEL
Date: 20240805

ACTIVE INGREDIENTS: STEMONA SESSILIFOLIA ROOT 50 g/100 mL
INACTIVE INGREDIENTS: BENZYL BENZOATE; CHLORHEXIDINE ACETATE; WATER; ALCOHOL; SOPHORA FLAVESCENS ROOT; DIBUTYL PHTHALATE; CNIDIUM MONNIERI FRUIT OIL

DOSAGE AND ADMINISTRATION

After washing your hair, spray an appropriate amount of liquid on the roots of your hair to moisten it

WARNINGS

1. Discontinue use for individuals with skin allergies.

2. Do not use this product when its characteristics have changed.

3. Children must use it under adult supervision.

4. Please keep this product out of reach of children.

INACTIVE INGREDIENT

BENZYL BENZOATE、CHLORHEXIDINE ACETATE、WATER 、ALCOHOL、SOPHORA FLAVESCENS ROOT、DIBUTYL PHTHALATE 、CNIDIUM MONNIERI FRUIT OIL

INDICATIONS AND USAGE

STEMONA JAPONICA WHOLE

KEEP OUT OF REACH OF CHILDREN

. Please keep this product out of reach of children.

PURPOSE

Spray on the roots of hair

PACKAGE LABEL

84422-102-01